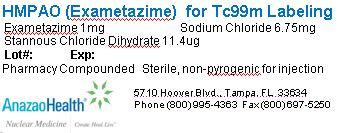 DRUG LABEL: Exametazime
NDC: 51808-214 | Form: INJECTION, POWDER, LYOPHILIZED, FOR SOLUTION
Manufacturer: AnazaoHealth Corporation
Category: prescription | Type: HUMAN PRESCRIPTION DRUG LABEL
Date: 20120701

ACTIVE INGREDIENTS: EXAMETAZIME 1 mg/1 1
INACTIVE INGREDIENTS: SODIUM CHLORIDE 6.75 mg/1 1; STANNOUS CHLORIDE 11.4 ug/1 1

Exametazime (HMPAO)
(for the preparation of Tc99m Exametazime injection)

Dear Medical Professional,

Per your order, we have compounded Exametazime as a sterile, freeze-dried preparation in a 10 mL vial. The characteristics of this preparation are described below

DESCRIPTION

AnazaoHealth’s compounded Exametazime vial is a sterile, non-pyrogenic preparation that consists of a lyophilized mixture of 1 mg of Exametazime, 6.75 mg of Sodium Chloride, 11.4 µg of Stannous Chloride Dihydrate and is maintained under an inert nitrogen atmosphere. The kit also contains a vial of Cobalt Chloride, which contains 0.3 mg of cobalt chloride hexahydrate, or Methylene Blue 1% (methylene blue 10 mg/mL) and Phosphate Buffer (monobasic sodium phosphate, sodium chloride, dibasic sodium phosphate This kit contains no antimicrobial preservative

CLINICAL PHARMACOLOGY

Cerebral Scintigraphy
When Exametazime is reconstituted with Tc99m pertechnetate, a lipophilic complex of Tc99m Exametazime is formed and is the active ingredient of the reconstituted product. The lipophilic complex crosses the blood-brain barrier. It converts to the less lipophilic complex 12% per hour. The preparation is good for 30 minutes without the use of a stabilizer. The in vitro addition of cobalt chloride helps to stabilize the complex for 6 hours.

Leukocyte (WBC) Labeling
The lipophilic complex of Tc99m Exametazime is taken up by leukocytes and selectively retained by neutrophils. Cobalt chloride, as a stabilizer, may be used with this procedure as well

INDICATIONS AND USAGE

Exametazime is a diagnostic agent used as an adjunct in the detection of altered cerebral perfusion in stroke patients and is also indicated for white blood cell labeling as an adjunct in the localization of abdominal infections and inflammatory bowel disease

PHYSICAL HALF-LIFE & TARGET ORGANS

The physical half-life of technetium, Tc99m, is 6 hours and has a principal radiation emission of gamma photons with a mean energy of 140 KeV.

CONTRAINDICATIONS

There are no known contraindications for this preparation.

DOSAGE AND ADMINISTRATION

Cerebral Scintigraphy

The recommended dose range for IV administration is 10 to 20 mCi (370 to 740 MBq).

Leukocyte (WBC) Labeling

The recommended dose range for IV administration is 7 to 25 mCi (259 to 925 MBq)

PREPARATION

For best results, use tc99m from a generator eluted within 24 hours. The eluate should be used within 2 hours of elution.

Reconstitution Instructions:

1. Snap off the plastic lid and place in appropriate lead shielding. Wipe the septum with 70% isopropyl alcohol and allow it to dry
2. Using a 10 mL syringe, draw up 15-80 mCi of tc99m. Dilute this to 7.5 mL with sterile preservative free saline and inject into the vial, being sure to withdraw an equal amount of gas from the vial to neutralize pressure.
3. Rock and invert the shielded vial for 10 seconds. Wait 2 minutes before adding stabilizer to allow for tagging.

- Add stabilizer to extend the length of time before use
- If no stabilizer is added, use the vial within 30 minutes.

Stabilizer Use:

Cobalt Chloride as a stabilizer: Wait 2 minutes after adding tc99m. Then add 3 mL of Cobalt Chloride to tc99m HMPAO. Solution is clear but slightly tan, which is normal. Swirl contents to mix and inspect solution for particulates. Draw 0.1 mL for a quality control sample. Solution is stable for 6 hours. This stabilizer can be used in WBC labeling

Methylene blue and Phosphate buffer as a stabilizer: Add 0.5 mL of 1% methylene blue to 4.5 mL of phosphate buffer solution. Swirl contents to mix then draw 3 mL and add to HMPAO within 2 minutes of mixing tc99m. Filter the final solution using a 0.22µm filter into an empty sterile vial. Draw 0.1 mL sample for quality control. Radiochemical purity must be 80% or higher. Solution is stable for 4 hours. This stabilizer is not recommended for use in WBC labeling

Storage and Handling

The preparation is recommended to be stored in the refrigerator at 2- 8(C (36 - 46(F)